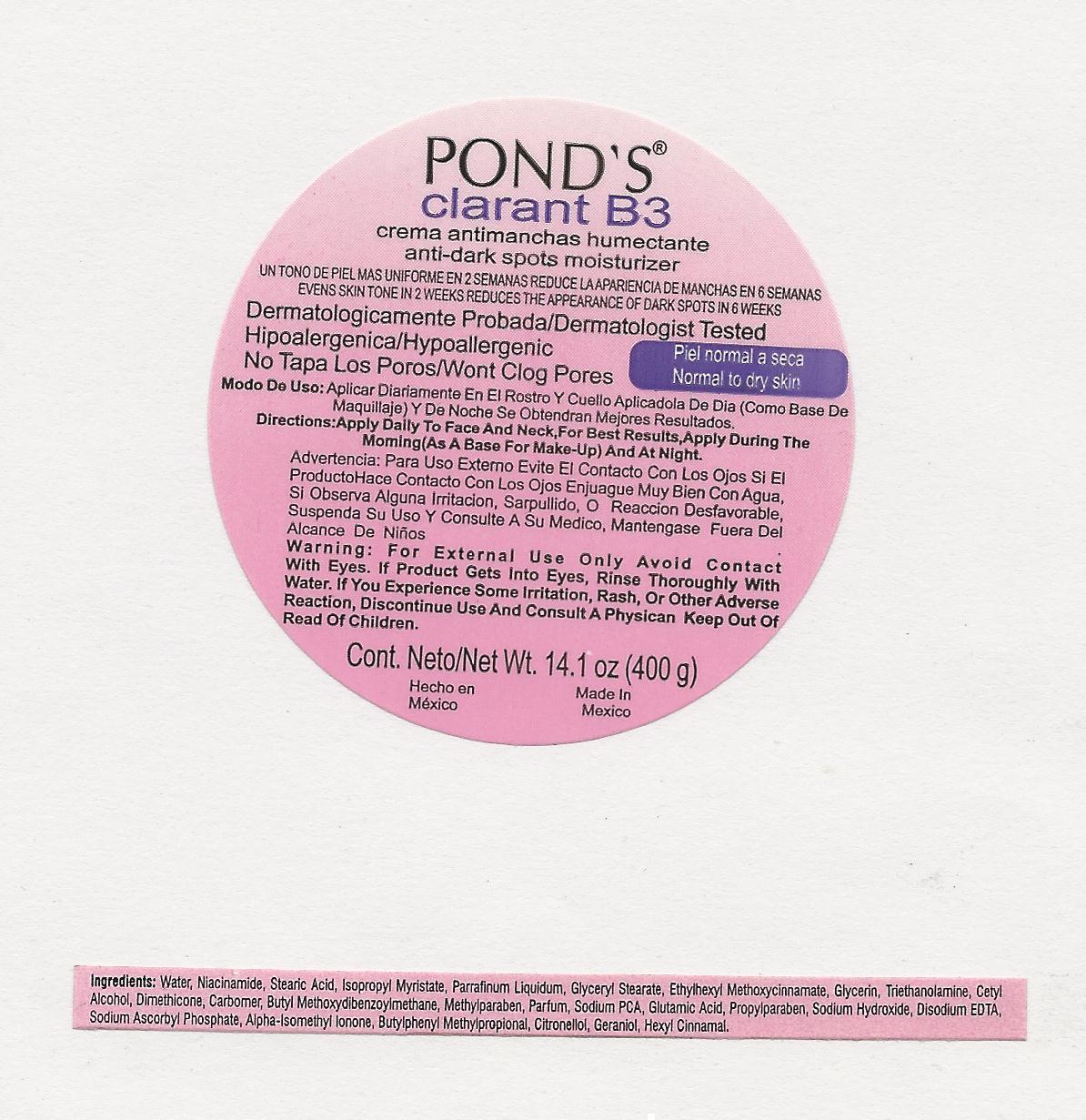 DRUG LABEL: PONDS
NDC: 51769-615 | Form: CREAM
Manufacturer: ALL NATURAL DYNAMICS
Category: otc | Type: HUMAN OTC DRUG LABEL
Date: 20130514

ACTIVE INGREDIENTS: AVOBENZONE 3 g/100 g
INACTIVE INGREDIENTS: Water; Niacinamide; Stearic Acid; Isopropyl Myristate; MINERAL OIL; GLYCERYL MONOSTEARATE; OCTINOXATE; Glycerin; TROLAMINE; CETOSTEARYL ALCOHOL; Dimethicone; Methylparaben; SODIUM PYRROLIDONE CARBOXYLATE; Glutamic Acid; Propylparaben; Sodium Hydroxide; EDETATE DISODIUM; SODIUM ASCORBYL PHOSPHATE; ISOMETHYL-.ALPHA.-IONONE; Butylphenyl Methylpropional; .BETA.-CITRONELLOL, (R)-; GERANIOL; .ALPHA.-HEXYLCINNAMALDEHYDE

Clarent B3

Ingredients:

Water, Myristic Acid, Stearic Acid, Niacinamide, Ethylhexyl Methoxycinnamate, Glycerin, Tapioca Starch, Triethanolamine, Cyclopentasiloxane, PEG/PPG-18/18 Dimethicone, Cetyl Alcohol, Butyl Methoxydibenzoylmethane, Phnoxyethanol, Fragrance, Carbomer, Acrylates Crosspolymer, Methylparaben, Propylparaben, Disodium EDTA, Sodium Ascorbyl Phosphate.

Directions:

Apply daily to ace and neck. For best results, apply during the morning (as a base for your make-up) and at night.

Warnings:

For external use only. Avoid contact with eyes. If product gets into eyes, rinse thoroughly with water.

Discontinue use and consult a physician:

If you experience some irritation, rash or other adverse reaction.

Keep out of reach of children.